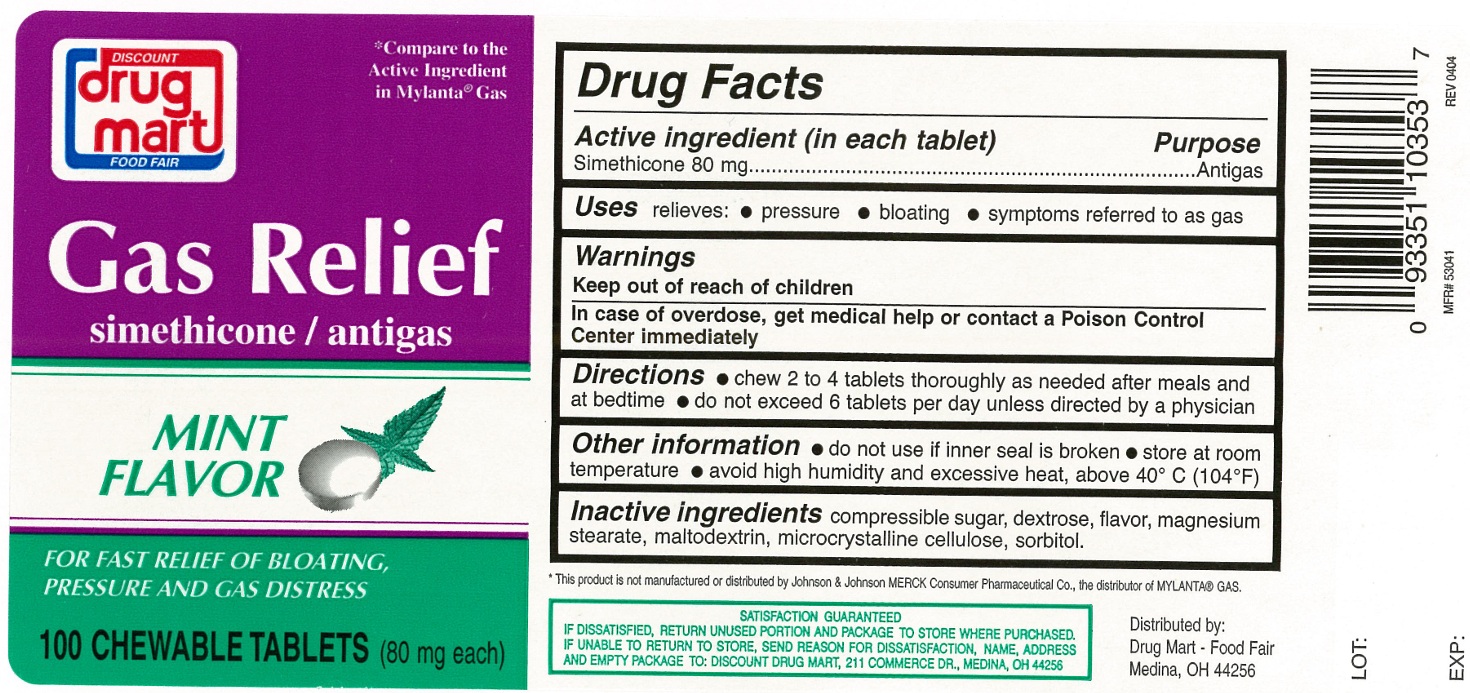 DRUG LABEL: Gas relief
NDC: 53943-301 | Form: TABLET, CHEWABLE
Manufacturer: Discount Drug Mart, Inc
Category: otc | Type: Human OTC Drug Label
Date: 20250220

ACTIVE INGREDIENTS: DIMETHICONE 80 mg/1 1
INACTIVE INGREDIENTS: SUGARCANE; MALTODEXTRIN; DEXTROSE, UNSPECIFIED FORM; MAGNESIUM STEARATE; MICROCRYSTALLINE CELLULOSE; SORBITOL

Gas Relief Chewable Tablets

ACTIVE INGREDIENT(in each tablet)

Simethicone 80 mg

PURPOSE

Antigas

USE(S)

relieves:

- pressure
- bloating
- symptoms referred to as gas

WARNINGS

.

KEEP OUT OF REACH OF CHILDREN

In case of overdose, get medical help or contact a Poison Control Center immediately.

DIRECTIONS

- chew 2 to 4 tablets thoroughly as needed after meals and at bedtime
- do not exceed 6 tablets per day unless directed by a physician

OTHER INFORMATION

- do not use if inner seal is broken
- store at room temperature
- avoid high humidity and excessive heat, above 40oC (104oF)

INACTIVE INGREDIENTS

compressible sugar, dextrose, flavor, magnesium stearate, maltodextrin, microcrystalline cellulose, sorbitol.

PRINCIPAL DISPLAY PANEL

DISCOUNT drug mart
FOOD FAIR

*Compare to the Active Ingredient in MYLANTA® GAS

NDC 53943-301-16

Gas Relief

simethicone/antigas

MINT FLAVOR
FOR FAST RELIEF OF BLOATING,
PRESSURE AND GAS DISTRESS

100 CHEWABLE TABLETS (80 mg each)